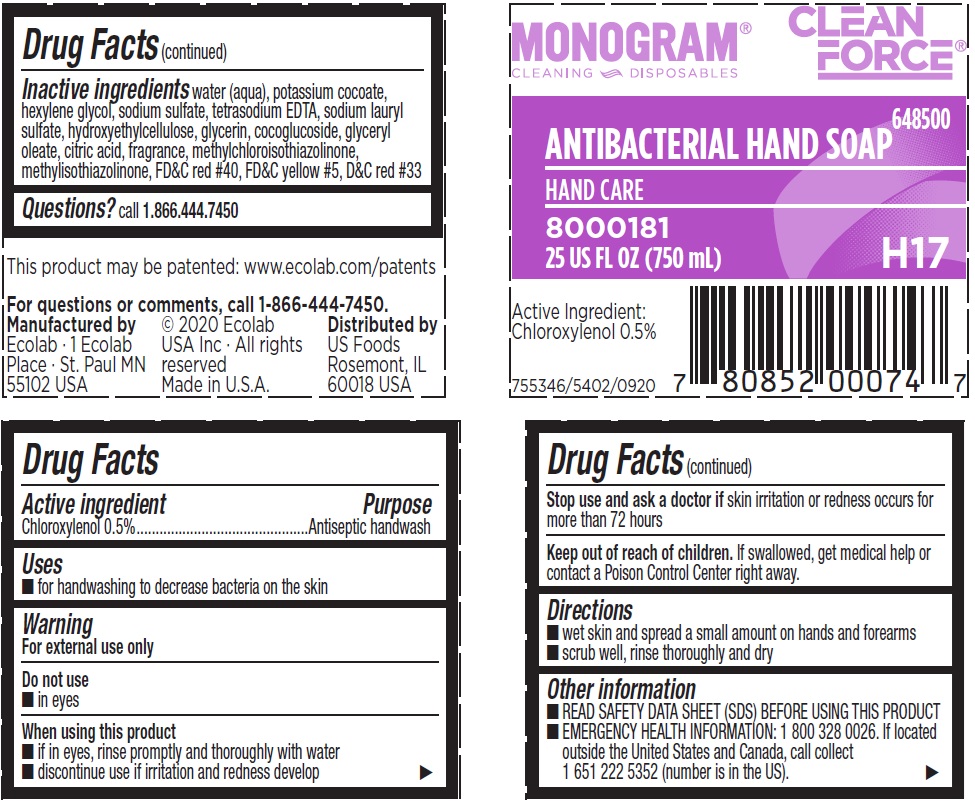 DRUG LABEL: Ecolab Clean Force
NDC: 47593-515 | Form: SOLUTION
Manufacturer: Ecolab Inc.
Category: otc | Type: HUMAN OTC DRUG LABEL
Date: 20251230

ACTIVE INGREDIENTS: CHLOROXYLENOL 5 mg/1 mL
INACTIVE INGREDIENTS: WATER; POTASSIUM COCOATE; HEXYLENE GLYCOL; SODIUM SULFATE; EDETATE SODIUM; SODIUM LAURYL SULFATE; HYDROXYETHYL CELLULOSE (3000 MPA.S AT 1%); GLYCERIN; COCO-GLUCOSIDE; GLYCERYL OLEATE; ANHYDROUS CITRIC ACID; METHYLCHLOROISOTHIAZOLINONE; METHYLISOTHIAZOLINONE; FD&C RED NO. 40; FD&C YELLOW NO. 5; D&C RED NO. 33

Drug Facts

Active ingredient

Chloroxylenol 0.5%

Purpose

Antiseptic handwash

Uses

- For handwashing to decrease bacteria on the skin

Warnings

For external use only

Do not use

- In eyes

When using this product

- If in eyes, rinse promptly and thoroughly with water
- Discontinue use if irritation and redness develop

Stop use and ask a doctor if skin irritation or redness occurs for more than 72 hours

Keep out of reach of children. If swallowed, get medical help or contact a Poison Control Center right away.

Directions

- Wet skin and spread a small amount on hands and forearms
- Scrub well, rinse thoroughly and dry

Other information

- READ SAFETY DATA SHEET (SDS) BEFORE USING THIS PRODUCT
- EMERGENCY HEALTH INFORMATION: 1 800 328 0026. If located outside the United States and Canada, call collect 1 651 222 5352 (number is in the US).

INACTIVE INGREDIENT

Inactive ingredients water (aqua), potassium cocoate, hexylene glycol, sodium sulfate, tetrasodium EDTA, sodium lauryl sulfate, hydroxyethylcellulose, glycerin, cocoglucoside, glyceryl oleate, citric acid, fragrance, methylchloroisothiazolinone, methylisothiazolinone, FD&C red #40, FD&C yellow #5, D&C red #33

Questions? call 1.866.444.7450

Representative label and principal display panel

MONOGRAM

CLEANING DISPOSABLES

CLEAN FORCE®

ANTIBACTERIAL HAND SOAP

648500

Hand care

8000181

25 FL OZ (750 mL)

H17

Active Ingredient: Chloroxylenol 0.5%

For questions or comments, call 1-866-444-7450.

Manufactured by | (c) 2020 Ecolab | Distributed by
Ecolab - 1 Ecolab | USA Inc - All rights | US Foods
Place - St. Paul MN | reserved | Rosemont, IL
55102 USA | Made in U.S.A. | 60018 USA